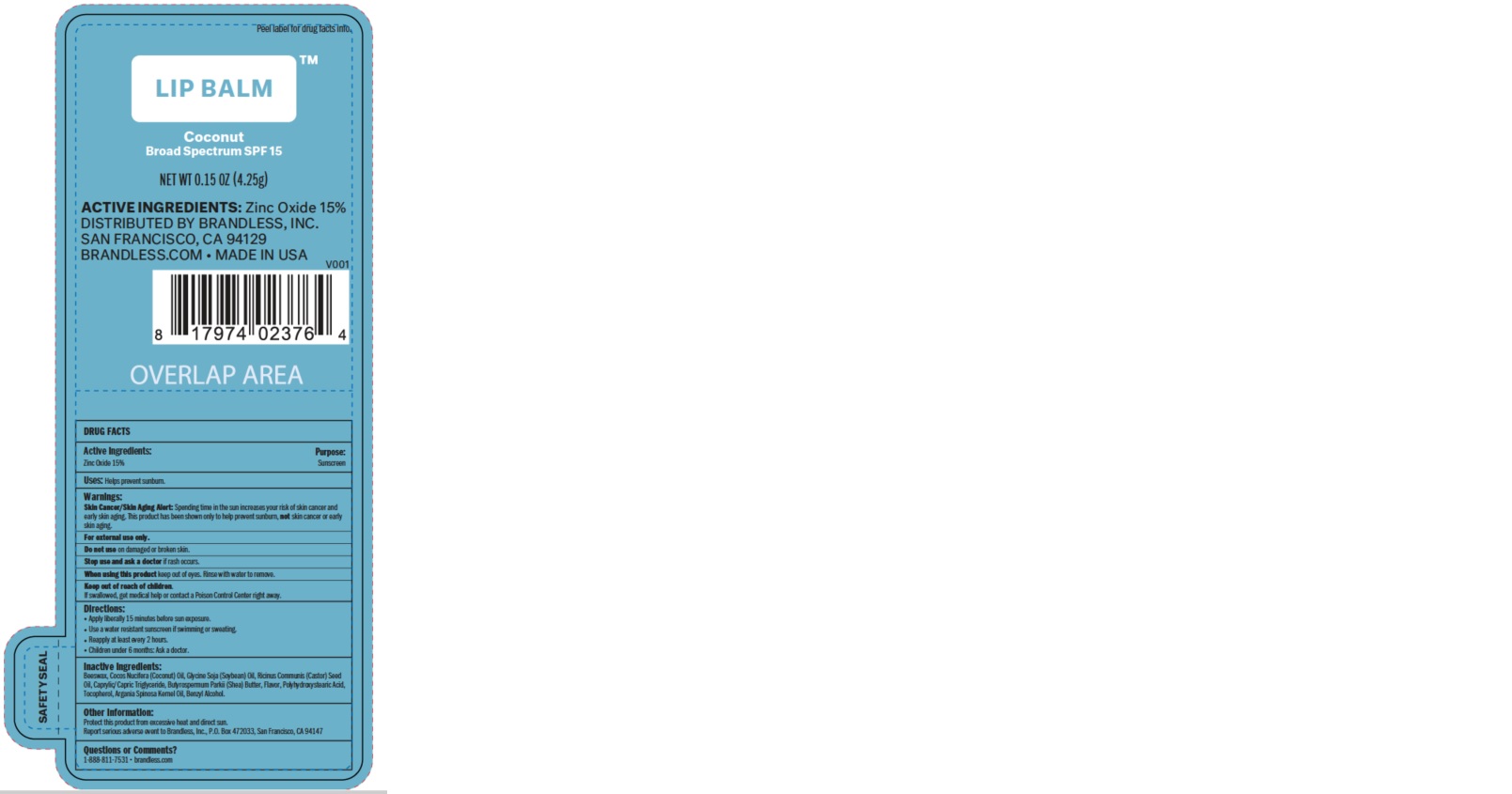 DRUG LABEL: Brandless Coconut Lip Balm SPF 15
NDC: 72599-2376 | Form: LIPSTICK
Manufacturer: Brandless
Category: otc | Type: HUMAN OTC DRUG LABEL
Date: 20181026

ACTIVE INGREDIENTS: ZINC OXIDE 15 g/100 g
INACTIVE INGREDIENTS: CASTOR OIL; MEDIUM-CHAIN TRIGLYCERIDES; SHEA BUTTER; ARGAN OIL; BENZYL ALCOHOL; YELLOW WAX; COCONUT OIL; SOYBEAN OIL; POLYHYDROXYSTEARIC ACID (2300 MW); TOCOPHEROL

Brandless Coconut Lip Balm SPF 15

Active ingredients

Zinc Oxide 15%

Purpose: Sunscreen

Uses

Helps prevent sunburn

Warnings

Skin Cancer/Skin Aging Alert: Spending time in the sun increases your risk of skin cancer and early skin aging. This product has been shown only to help prevent sunburn, not skin cancer or early skin aging.

For external use only.

Do not use on damaged or broken skin.

Stop use and ask a doctor if rash occurs.

When using this product keep out of eyes. Rinse with water to remove.

Keep out of the reach of children. If swallowed, get medical help or contact a Poison Control Center right away.

Directions

- apply liberally 15 minutes before sun exposure
- use a water resistant sunscreen if swimming or sweating
- reapply at least every 2 hours
- children under 6 months: Ask a doctor.

Inactive ingredients

Beeswax, Cocos Nucifera (Coconut) Oil, Glycine Soja (Soybean) Oil, Ricinus Communis (Castor) Seed Oil, Caprylic/Capric Triglyceride, Butyrospermum Parkii (Shea) Butter, Flavor, Polyhydroxystearic Acid, Tocopherol, Argania Spinosa Kernel Oil, Benzyl Alcohol.

Other information

Protect this product from excessive heat and direct sun

Report serious adverse event to Brandless, Inc., P.O. Box 472033, San Francisco, CA 94147

Questions or Comments?

1-888-811-7531

Brandless.com

Company information

Distributed by Brandless, Inc. San Francisco, CA 94129

Brandless.com

Product Packaging

Brandless Lip Balm

Coconut

Broad Spectrum SPF 15

NET WT 0.15 OZ (4.25g)